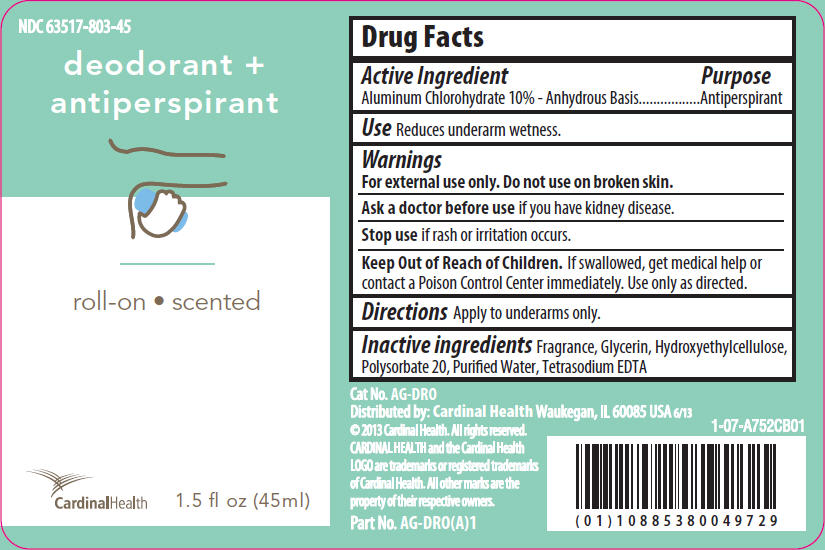 DRUG LABEL: Roll On Anti-Perspirant (Alcohol Free)
NDC: 63517-803 | Form: SOLUTION
Manufacturer: Cardinal Health
Category: otc | Type: HUMAN OTC DRUG LABEL
Date: 20260112

ACTIVE INGREDIENTS: ALUMINUM CHLOROHYDRATE 10 g/100 mL
INACTIVE INGREDIENTS: WATER; HYDROXYETHYL CELLULOSE (2000 MPA.S AT 1%); GLYCERIN; POLYSORBATE 20; EDETATE SODIUM

Roll-On Anti-Perspirant

Drug Facts

Active Ingredient

Aluminum Chlorohydrate 10% - Anhydrous Basis

Purpose

Antiperspirant

Use

Reduces underarm wetness.

Warnings

Ask a doctor before useif you have kidney disease.

Stop useif rash or irritation occurs.

Keep Out of Reach of Children.If swallowed, get medical help or contact a Poison Control Center immediately. Use only as directed.

Directions

Apply to underarms only.

Inactive ingredients

Fragrance, Glycerin, Hydroxyethylcellulose, Polysorbate 20, Purified Water, Tetrasodium EDTA

PRINCIPAL DISPLAY PANEL

NDC 63517-803-45

deodorant +
antiperspirant

roll-on • scented

CardinalHealth

1.5 fl oz (45ml)